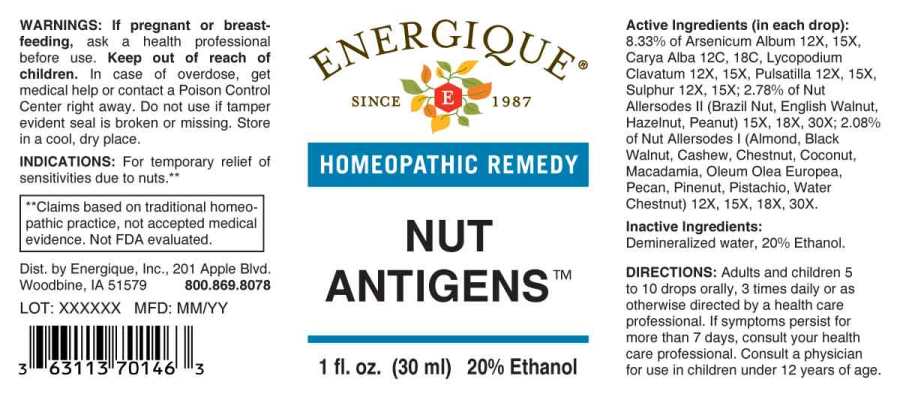 DRUG LABEL: Nut Antigens
NDC: 44911-0402 | Form: LIQUID
Manufacturer: Energique, Inc.
Category: homeopathic | Type: HUMAN OTC DRUG LABEL
Date: 20241029

ACTIVE INGREDIENTS: ALMOND 12 [hp_X]/1 mL; CASHEW 12 [hp_X]/1 mL; BLACK WALNUT 12 [hp_X]/1 mL; PECAN 12 [hp_X]/1 mL; COCONUT 12 [hp_X]/1 mL; OLIVE OIL 12 [hp_X]/1 mL; CHINESE CHESTNUT 12 [hp_X]/1 mL; TRAPA BICORNIS SEED 12 [hp_X]/1 mL; PINE NUT 12 [hp_X]/1 mL; MACADAMIA NUT 12 [hp_X]/1 mL; PISTACHIO 12 [hp_X]/1 mL; PEANUT 15 [hp_X]/1 mL; ENGLISH WALNUT 15 [hp_X]/1 mL; BRAZIL NUT 15 [hp_X]/1 mL; AMERICAN HAZELNUT 15 [hp_X]/1 mL; ARSENIC TRIOXIDE 12 [hp_X]/1 mL; LYCOPODIUM CLAVATUM SPORE 12 [hp_X]/1 mL; PULSATILLA VULGARIS WHOLE 12 [hp_X]/1 mL; SULFUR 12 [hp_X]/1 mL; MOCKERNUT 12 [hp_C]/1 mL
INACTIVE INGREDIENTS: WATER; ALCOHOL

DRUG FACTS:

ACTIVE INGREDIENTS:

(in each drop): 8.33% of Arsenicum Album 12X, 15X, Carya Alba 12C, 18C, Lycopodium Clavatum 12X, 15X, Pulsatilla (Vulgaris) 12X, 15X, Sulphur 12X, 15X; 2.78% of Brazil Nut (Nut) 15X, 18X, 30X, English Walnut (Nut) 15X, 18X, 30X, Hazelnut (Nut) 15X, 18X, 30X, Peanut (Nut) 15X, 18X, 30X; 2.08% of Almond (Nut) 12X, 15X, 18X, 30X, Black Walnut (Nut) 12X, 15X, 18X, 30X, Cashew (Nut) 12X, 15X, 18X, 30X, Chestnut (Nut) 12X, 15X, 18X, 30X, Coconut 12X, 15X, 18X, 30X, Macadamia (Nut) 12X, 15X, 18X, 30X, Oleum Olea Europaea 12X, 15X, 18X, 30X, Pecan (Nut) 12X, 15X, 18X, 30X, Pinenut (Nut) 12X, 15X, 18X, 30X, Pistachio (Nut) 12X, 15X, 18X, 30X, Water Chestnut (Nut) 12X, 15X, 18X, 30X.

INDICATIONS:

For temporary relief of sensitivities due to nuts.**

**Claims based on traditional homeopathic practice, not accepted medical evidence. Not FDA evaluated.

WARNINGS:

If pregnant or breastfeeding, ask a health professional before use.

Keep out of reach of children. In case of overdose, get medical help or contact a Poison Control Center right away.

Do not use if tamper evident seal is broken or missing.

Store in a cool, dry place.

Keep out of reach of children. In case of overdose, get medical help or contact a Poison Control Center right away.

DIRECTIONS:

Adults and children 5 to 10 drops orally, 3 times daily or as otherwise directed by a health care professional. If symptoms persist for more than 7 days, consult your health care professional. Consult a physician for use in children under 12 years of age.

INDICATIONS:

For temporary relief of sensitivities due to nuts.**

**Claims based on traditional homeopathic practice, not accepted medical evidence. Not FDA evaluated.

INACTIVE INGREDIENTS:

Demineralized water, 20% Ethanol.

QUESTIONS:

Dist. by Energique, Inc.

201 Apple Blvd.

Woodbine, IA 51579 800.869.8078

PACKAGE LABEL DISPLAY:

ENERGIQUE

SINCE 1987

HOMEOPATHIC REMEDY

NUT

ANTIGENS

1 fl. oz. (30 ml)